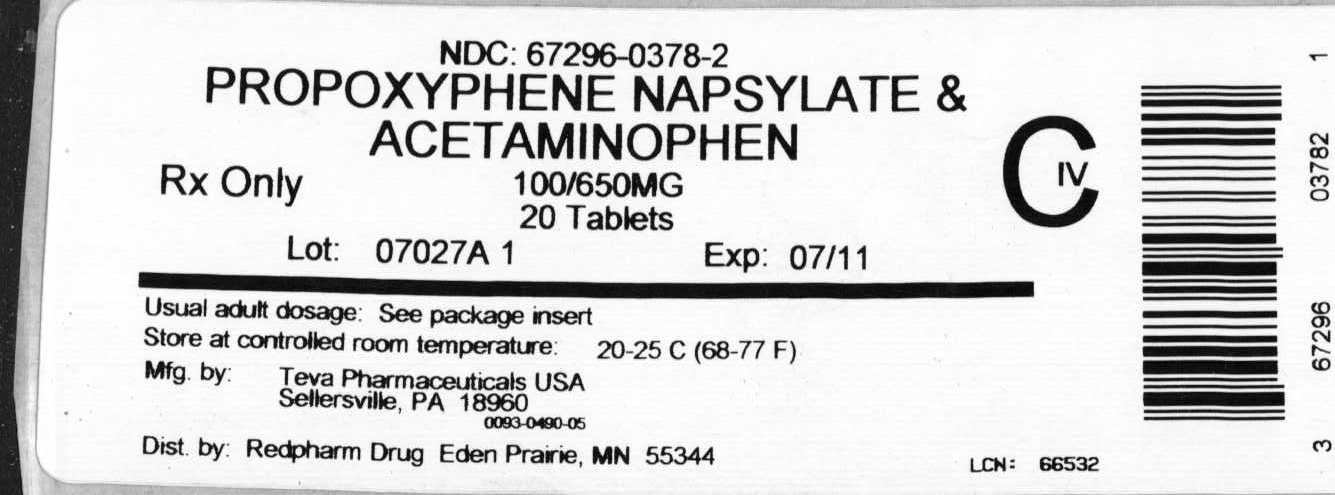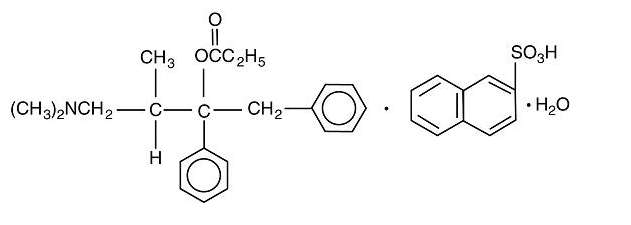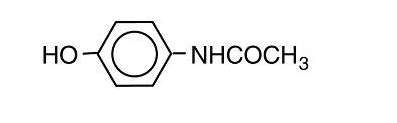 DRUG LABEL: Propoxyphene Napsylate and Acetaminophen
NDC: 67296-0378 | Form: TABLET, FILM COATED
Manufacturer: RedPharm Drug Inc.
Category: prescription | Type: HUMAN PRESCRIPTION DRUG LABEL
Date: 20110525
DEA Schedule: CIV

ACTIVE INGREDIENTS: PROPOXYPHENE NAPSYLATE 100 mg/1 1; ACETAMINOPHEN 650 mg/1 1
INACTIVE INGREDIENTS: CASTOR OIL; COLLOIDAL SILICON DIOXIDE; HYPROMELLOSES; MAGNESIUM STEARATE; CELLULOSE, MICROCRYSTALLINE; POVIDONE; STARCH, CORN; STEARIC ACID; CROSPOVIDONE

PROPOXYPHENE NAPSYLATE AND ACETAMINOPHEN TABLETS, USP 100 mg/650 mg CIV
0490
0890
Rx only

WARNINGS

- There have been numerous cases of accidental and intentional overdose with propoxyphene products either alone or in combination with other CNS depressants, including alcohol. Fatalities within the first hour of overdosage are not uncommon. Many of the propoxyphene-related deaths have occurred in patients with previous histories of emotional disturbances or suicidal ideation/attempts and/or concomitant administration of sedatives, tranquilizers, muscle relaxants, antidepressants, or other CNS-depressant drugs. Do not prescribe propoxyphene for patients who are suicidal or have a history of suicidal ideation.
- The metabolism of propoxyphene may be altered by strong CYP3A4 inhibitors (such as ritonavir, ketoconazole, itraconazole, troleandomycin, clarithromycin, nelfinavir, nefazadone, amiodarone, amprenavir, aprepitant, diltiazem, erythromycin, fluconazole, fosamprenavir, grapefruit juice, and verapamil) leading to enhanced propoxyphene plasma levels. Patients receiving propoxyphene and any CYP3A4 inhibitor should be carefully monitored for an extended period of time and dosage adjustments should be made if warranted (see CLINICAL PHARMACOLOGY, Drug Interactions; WARNINGS; PRECAUTIONS; and DOSAGE AND ADMINISTRATION for further information).

DESCRIPTION

Propoxyphene napsylate and acetaminophen tablets USP contain propoxyphene napsylate and acetaminophen.

Propoxyphene napsylate is an odorless, white crystalline powder with a bitter taste. It is very slightly soluble in water, soluble in methanol, in ethanol, in chloroform, and in acetone. Chemically it is (αS,1R)-α-[2-(dimethylamino)-1-methylethyl]-α-phenylphenethyl propionate compound with 2-naphthalenesulfonic acid (1:1) monohydrate and can be represented by the following structural formula:

C22H29NO2•C10H8O3S•H2O M.W. 565.74

Propoxyphene napsylate differs from propoxyphene hydrochloride in that it allows more stable liquid dosage forms and tablet formulations. Because of differences in molecular weight, a dose of 100 mg (176.8 μmol) of propoxyphene napsylate is required to supply an amount of propoxyphene equivalent to that present in 65 mg (172.9 μmol) of propoxyphene hydrochloride.

Acetaminophen, 4'-hydroxyacetanilide, is a non-opiate, non-salicylate analgesic and antipyretic which occurs as a white, odorless, crystalline powder, possessing a slightly bitter taste. Chemically, it is acetamide, N-(4-hydroxyphenyl)- and can structurally be represented by the following:

C8H9NO2 M.W. 151.16

Each pink or white tablet of propoxyphene napsylate and acetaminophen tablets contains 100 mg propoxyphene napsylate and 650 mg acetaminophen.

Propoxyphene napsylate and acetaminophen tablets, USP 100 mg/650 mg (PINK) contain the following inactive ingredients: colloidal silicon dioxide, D&C red No. 27 aluminum lake, D&C yellow No. 10 aluminum lake, hydroxypropyl cellulose, hypromellose, magnesium stearate, microcrystalline cellulose, polyethylene glycol, povidone, pregelatinized starch, stearic acid, titanium dioxide, and crospovidone.

Propoxyphene napsylate and acetaminophen tablets, USP 100 mg/650 mg (WHITE) contain the following inactive ingredients: castor oil, colloidal silicon dioxide, hypromellose, magnesium stearate, microcrystalline cellulose, povidone, pregelatinized starch, stearic acid, and crospovidone.

CLINICAL PHARMACOLOGY

Pharmacology

Propoxyphene is a centrally acting opiate analgesic. In vitro studies demonstrated propoxyphene and the metabolite norpropoxyphene inhibit sodium channels (local anesthetic effect) with norpropoxyphene being approximately 2 fold more potent than propoxyphene and propoxyphene approximately 10 fold more potent than lidocaine. Propoxyphene and norpropoxyphene inhibit the voltage-gated potassium current carried by cardiac rapidly activating delayed rectifier (hERG) channels with approximately equal potency. It is unclear if the effects on ion channels occur within therapeutic dose range.

Acetaminophen is a non-opiate, non-salicylate analgesic and antipyretic. The site and mechanism for the analgesic effect of acetaminophen has not been determined. The antipyretic effect of acetaminophen is mediated through activity in the hypothalamic heat-regulating centers. Acetaminophen inhibits prostaglandin synthetase. Therapeutic doses of acetaminophen have negligible effects on the cardiovascular or respiratory systems; however, toxic doses may cause circulatory failure and rapid, shallow breathing.

Pharmacokinetics

Absorption

Peak plasma concentrations of propoxyphene are reached in 2 to 2.5 h. After a 65 mg oral dose of propoxyphene hydrochloride, peak plasma levels of 0.05 to 0.1 mcg/mL for propoxyphene and 0.1 to 0.2 mcg/mL for norpropoxyphene (major metabolite) are achieved. Repeated doses of propoxyphene at 6 h intervals lead to increasing plasma concentrations, with a plateau after the ninth dose at 48 h. Propoxyphene has a half-life of 6 to 12 h, whereas that of norpropoxyphene is 30 to 36 h.

Acetaminophen is absorbed from the gastrointestinal tract and has a plasma half-life of 1.25 to 3 h, which may be increased by liver damage and following overdosage.

Distribution

Propoxyphene is about 80% bound to proteins and has a large volume of distribution, 16 L/kg.

Acetaminophen is relatively uniformly distributed throughout most body fluids. Binding of the drug to plasma proteins is variable; only 20% to 50% may be bound at the concentrations encountered during acute intoxication.

Metabolism

Propoxyphene undergoes extensive first-pass metabolism by intestinal and hepatic enzymes. The major route of metabolism is cytochrome CYP3A4 mediated N-demethylation to norpropoxyphene, which is excreted by the kidneys. Ring hydroxylation and glucuronide formation are minor metabolic pathways.

Acetaminophen is extensively metabolized in the liver. Less than 5% of acetaminophen dose is excreted unchanged in the kidney. About 85% of an acetaminophen dose is metabolized by conjugation, mainly glucuronidation via UDP-glucuronosyltransferase (mainly UGT1A6) and to a lesser extent sulfation via sulfotransferase (mainly SLT1A1 and SLT1A3). The glucuronide and sulfate conjugates are nontoxic and are largely excreted in the urine and bile. About 8 to 10% of an acetaminophen dose is oxidized by cytochrome CYP2E1 to form the toxic reactive intermediate, N-acetyl-p-benzoquinone imine (NAPQI). NAPQI is further metabolized via glutathione (GSH) conjugation, yielding non-toxic thiol metabolites including cysteine, mercapturate, methylthioacetaminophen, and methanesulfinylacetaminophen that are excreted in the urine. Acetaminophen is also oxidized at a low percentage by cytochrome CYP2A6 to form inert catechols (e.g., methoxyacetaminophen).

Excretion

In 48 h, approximately 20 to 25% of the administered dose of propoxyphene is excreted via the urine, most of which is free or conjugated norpropoxyphene. The renal clearance rate of propoxyphene is 2.6 L/min.

Elimination of acetaminophen is principally by liver metabolism (conjugation) and subsequent renal excretion of metabolites. Approximately 85% of an oral dose appears in the urine within 24 hours of administration, most as the glucuronide conjugate, with small amounts of other conjugates and unchanged drug.

SPECIAL POPULATIONS

Geriatric Patients

After oral administration of propoxyphene in elderly patients (70 to 78 years), much longer half-lives of propoxyphene and norpropoxyphene have been reported (propropoxyphene 13 to 35 h, norpropoxyphene 22 to 41 h). In addition, the AUC was an average of 3 fold higher and the Cmax was an average of 2.5 fold higher in the elderly when compared to a younger (20 to 28 years) population. Longer dosage intervals may be considered in the elderly because the metabolism of propoxyphene may be reduced in this patient population. After multiple oral doses of propoxyphene in elderly patients (70 to 78 years), the Cmax of the metabolite (norpropoxyphene) was increased 5 fold.

Pediatric Patients

Neither propoxyphene alone nor in combination with acetaminophen has been studied in pediatric patients.

Hepatic Impairment

No formal pharmacokinetic study of either propoxyphene alone or in combination with acetaminophen has been conducted in patients with mild, moderate or severe hepatic impairment.

After oral administration of propoxyphene in patients with cirrhosis, plasma concentrations of propoxyphene were considerably higher and norpropoxyphene concentrations were much lower than in control patients. This is presumably because of a decreased first-pass metabolism of orally administered propoxyphene in these patients. The AUC ratio of norpropoxyphene: propoxyphene was significantly lower in patients with cirrhosis (0.5 to 0.9) than in controls (2.5 to 4).

Compared to healthy subjects, acetaminophen had a lower total clearance and longer half-life in patients with liver disease. Decreased metabolite formation clearance (8 to 42%) was observed in subjects with liver disease compared to healthy subjects after both single and multiple-doses (at steady state). In addition, there is an increase in the amount of acetaminophen excreted unchanged in the urine (4.7% vs. 2.5%) in patients with liver disease compared to healthy subjects after repeat doses, suggesting that more acetaminophen was excreted by renal elimination in the liver disease state.

Renal Impairment

No formal pharmacokinetic study of either propoxyphene alone or in combination with acetaminophen has been conducted in patients with mild, moderate or severe renal impairment.

After oral administration of propoxyphene in anephric patients, the AUC and Cmax values were an average of 76% and 88% greater, respectively. Dialysis removes only insignificant amounts (8%) of administered dose of propoxyphene.

Drug Interactions

The metabolism of propoxyphene may be altered by strong CYP3A4 inhibitors (such as ritonavir, ketoconazole, itraconazole, troleandomycin, clarithromycin, nelfinavir, nefazadone, amiodarone, amprenavir, aprepitant, diltiazem, erythromycin, fluconazole, fosamprenavir, grapefruit juice, and verapamil) leading to enhanced propoxyphene plasma levels. On the other hand, strong CYP3A4 inducers such as rifampin may lead to enhanced metabolite (norpropoxyphene) levels.

Propoxyphene is also thought to possess CYP3A4 and CYP2D6 enzyme inhibiting properties. Coadministration with a drug that is a substrate of CYP3A4 or CYP2D6, may result in higher plasma concentrations and increased pharmacologic or adverse effects of that drug.

CLINICAL STUDIES

The efficacy of propoxyphene in combination with acetaminophen was studied in seven single-dose, randomized, double-blind, placebo-controlled trials in patients with mild to severe postpartum pain. One of the studies demonstrated that both propoxyphene and acetaminophen in the combination contributed to a greater reduction in pain than acetaminophen and propoxyphene alone and that propoxyphene was superior to placebo.

There is insufficient information available to assess efficacy of propoxyphene in combination with acetaminophen in patients with chronic pain.

INDICATIONS AND USAGE

Propoxyphene napsylate and acetaminophen tablets are indicated for the relief of mild to moderate pain.

CONTRAINDICATIONS

Propoxyphene napsylate and acetaminophen tablets are contraindicated in patients with known hypersensitivity to propoxyphene or acetaminophen.

Propoxyphene napsylate and acetaminophen tablets are contraindicated in patients with significant respiratory depression (in unmonitored settings or the absence of resuscitative equipment) and patients with acute or severe asthma or hypercarbia.

Propoxyphene napsylate and acetaminophen tablets are contraindicated in any patient who has or is suspected of having paralytic ileus.

WARNINGS

Risk of Overdose

There have been numerous cases of accidental and intentional overdose with propoxyphene products either alone or in combination with other CNS depressants, including alcohol. Fatalities within the first hour of overdosage are not uncommon. Many of the propoxyphene-related deaths have occurred in patients with previous histories of emotional disturbances or suicidal ideation/attempts and/or concomitant administration of sedatives, tranquilizers, muscle relaxants, antidepressants, or other CNS-depressant drugs. Do not prescribe propoxyphene for patients who are suicidal or have a history of suicidal ideation.

Respiratory Depression

Respiratory depression is the chief hazard from all opioid agonist preparations. Respiratory depression occurs most frequently in elderly or debilitated patients, usually following large initial doses in non-tolerant patients, or when opioids are given in conjunction with other agents that depress respiration. Propoxyphene napsylate and acetaminophen tablets should be used with extreme caution in patients with significant chronic obstructive pulmonary disease or cor pulmonale, and in patients having substantially decreased respiratory reserve, hypoxia, hypercapnia, or preexisting respiratory depression. In such patients, even usual therapeutic doses of propoxyphene napsylate and acetaminophen tablets may decrease respiratory drive to the point of apnea. In these patients alternative non-opioid analgesics should be considered, and opioids should be employed only under careful medical supervision at the lowest effective dose.

Hypotensive Effect

Propoxyphene napsylate and acetaminophen tablets, like all opioid analgesics, may cause severe hypotension in an individual whose ability to maintain blood pressure has been compromised by a depleted blood volume, or after concurrent administration with drugs such as phenothiazines or other agents which compromise vasomotor tone. Propoxyphene napsylate and acetaminophen tablets may produce orthostatic hypotension in ambulatory patients. Propoxyphene napsylate and acetaminophen tablets, like all opioid analgesics, should be administered with caution to patients in circulatory shock, since vasodilatation produced by the drug may further reduce cardiac output and blood pressure.

Head Injury and Increased Intracranial Pressure

The respiratory depressant effects of narcotics and their capacity to elevate cerebrospinal fluid pressure may be markedly exaggerated in the presence of head injury, other intracranial lesions or a preexisting increase in intracranial pressure. Furthermore, narcotics produce adverse reactions which may obscure the clinical course of patients with head injuries.

Drug Interactions

The concomitant use of propoxyphene and CNS depressants, including alcohol, can result in potentially serious adverse events including death. Because of its added depressant effects, propoxyphene should be prescribed with caution for those patients whose medical condition requires the concomitant administration of sedatives, tranquilizers, muscle relaxants, antidepressants, or other CNS-depressant drugs.

Usage in Ambulatory Patients

Propoxyphene may impair the mental and/or physical abilities required for the performance of potentially hazardous tasks, such as driving a car or operating machinery. The patient should be cautioned accordingly.

Use With Other Acetaminophen-Containing Agents

Due to the potential for acetaminophen hepatotoxicity at doses higher than the recommended dose, propoxyphene napsylate and acetaminophen tablets should not be used concomitantly with other acetaminophen-containing products.

Use With Alcohol

Hepatotoxicity and severe hepatic failure occurred in chronic alcoholics following therapeutic doses of acetaminophen. Patients should be cautioned about the concomitant use of propoxyphene products and alcohol because of potentially serious CNS-additive effects of these agents that can lead to death.

PRECAUTIONS

Tolerance and Physical Dependence

Tolerance is the need for increasing doses of opioids to maintain a defined effect such as analgesia (in the absence of disease progression or other external factors). Physical dependence is manifested by withdrawal symptoms after abrupt discontinuation of a drug or upon administration of an antagonist. Physical dependence and tolerance are not unusual during chronic opioid therapy.

The opioid abstinence or withdrawal syndrome is characterized by some or all of the following: restlessness, lacrimation, rhinorrhea, yawning, perspiration, chills, myalgia, and mydriasis. Other symptoms also may develop, including: irritability, anxiety, backache, joint pain, weakness, abdominal cramps, insomnia, nausea, anorexia, vomiting, diarrhea, or increased blood pressure, respiratory rate, or heart rate. In general, opioids should not be abruptly discontinued (see DOSAGE AND ADMINISTRATION, Cessation of Therapy).

If propoxyphene napsylate and acetaminophen tablets are abruptly discontinued in a physically dependent patient, an abstinence syndrome may occur (see DRUG ABUSE AND DEPENDENCE). If signs and symptoms of withdrawal occur, patients should be treated by reinstitution of opioid therapy followed by gradual tapered dose reduction of propoxyphene napsylate and acetaminophen tablets combined with symptomatic support (see DOSAGE AND ADMINISTRATION, Cessation of Therapy).

Use in Pancreatic/Biliary Tract Disease

Propoxyphene napsylate and acetaminophen tablets may cause spasm of the sphincter of Oddi and should be used with caution in patients with biliary tract disease, including acute pancreatitis. Opioids like propoxyphene napsylate and acetaminophen tablets may cause increases in the serum amylase level.

Hepatic or Renal Impairment

Insufficient information exists to make appropriate dosing recommendations regarding the use of either propoxyphene alone or in combination with acetaminophen in patients with hepatic or renal impairment as a function of degree of impairment. Higher plasma concentrations and/or delayed elimination may occur in case of impaired hepatic function and/or impaired renal function (see CLINICAL PHARMACOLOGY). If the drug is used in these patients, it should be used with caution because of the hepatic metabolism of propoxyphene and acetaminophen and renal excretion of their metabolites.

Information for Patients/Caregivers

1. Patients should be advised to report pain and adverse experiences occurring during therapy. Individualization of dosage is essential to make optimal use of this medication.
2. Patients should be advised not to adjust the dose of propoxyphene napsylate and acetaminophen tablets without consulting the prescribing professional.
3. Patients should be advised that propoxyphene napsylate and acetaminophen tablets may impair mental and/or physical ability required for the performance of potentially hazardous tasks (e.g., driving, operating heavy machinery).
4. Patients should not combine propoxyphene napsylate and acetaminophen tablets with central nervous system depressants (e.g., sleep aids, tranquilizers) except by the orders of the prescribing physician, because additive effects may occur.
5. Patients should be instructed not to consume alcoholic beverages, including prescription and over-the-counter medications that contain alcohol, while using propoxyphene napsylate and acetaminophen tablets because of risk of serious adverse events including death.
6. Women of childbearing potential who become, or are planning to become, pregnant should be advised to consult their physician regarding the effects of analgesics and other drug use during pregnancy on themselves and their unborn child.
7. Patients should be advised that propoxyphene napsylate and acetaminophen tablets are a potential drug of abuse. They should protect it from theft, and it should never be given to anyone other than the individual for whom it was prescribed.
8. Patients should be advised that if they have been receiving treatment with propoxyphene napsylate and acetaminophen tablets for more than a few weeks and cessation of therapy is indicated, it may be appropriate to taper the propoxyphene napsylate and acetaminophen tablet dose, rather than abruptly discontinue it, due to the risk of precipitating withdrawal symptoms. Their physician can provide a dose schedule to accomplish a gradual discontinuation of the medication.
9. Instruct patients not to consume any other medication that contain acetaminophen, including acetaminophen-based over-the-counter medications, while taking propoxyphene napsylate and acetaminophen tablets.

Drug Interactions With Propoxyphene

Propoxyphene is metabolized mainly via the human cytochrome P450 3A4 isoenzyme system (CYP3A4), therefore potential interactions may occur when propoxyphene is administered concurrently with agents that affect CYP3A4 activity.

The metabolism of propoxyphene may be altered by strong CYP3A4 inhibitors (such as ritonavir, ketoconazole, itraconazole, troleandomycin, clarithromycin, nelfinavir, nefazadone, amiodarone, amprenavir, aprepitant, diltiazem, erythromycin, fluconazole, fosamprenavir, grapefruit juice, and verapamil) leading to enhanced propoxyphene plasma levels. Coadministration with agents that induce CYP3A4 activity may reduce the efficacy of propoxyphene. Strong CYP3A4 inducers such as rifampin may lead to enhanced metabolite (norpropoxyphene) levels.

Propoxyphene is also thought to possess CYP3A4 and CYP2D6 enzyme inhibiting properties and coadministration with drugs that rely on either of these enzymes for metabolism may result in increased pharmacologic or adverse effects of that drug. Severe neurologic signs, including coma, have occurred with concurrent use of carbamazepine (metabolized by CYP3A4).

Increased risk of bleeding has been observed with warfarin-like agents when given along with propoxyphene; however, the mechanistic basis of this interaction is unknown.

CNS Depressants

Patients receiving narcotic analgesics, general anesthetics, phenothiazines, other tranquilizers, sedative-hypnotics or other CNS depressants (including alcohol) concomitantly with propoxyphene napsylate and acetaminophen tablets may exhibit an additive CNS depression. Interactive effects resulting in respiratory depression, hypotension, profound sedation, or coma may result if these drugs are taken in combination with the usual dosage of propoxyphene napsylate and acetaminophen tablets. When such combined therapy is contemplated, the dose of one or both agents should be reduced.

Mixed Agonist/Antagonist Opioid Analgesics

Agonist/antagonist analgesics (i.e., pentazocine, nalbuphine, butorphanol and buprenorphine) should be administered with caution to patients who have received or are receiving a course of therapy with a pure opioid agonist analgesic such as propoxyphene napsylate and acetaminophen tablets. In this situation, mixed agonist/antagonist analgesics may reduce the analgesic effect of propoxyphene napsylate and acetaminophen tablets and/or may precipitate withdrawal symptoms in these patients.

Monoamine Oxidase Inhibitors (MAOIs)

MAOIs have been reported to intensify the effects of at least one opioid drug causing anxiety, confusion and significant depression of respiration or coma. The use of propoxyphene napsylate and acetaminophen tablets is not recommended for patients taking MAOIs or within 14 days of stopping such treatment.

Drug Interactions With Acetaminophen

Alcohol: Hepatotoxicity has occurred in chronic alcoholics following various dose levels (moderate to excessive) of acetaminophen.

Anticholinergics: The onset of acetaminophen effect may be delayed or decreased slightly, but the ultimate pharmacological effect is not significantly affected by anticholinergics.

Oral Contraceptives: Increase in glucuronidation resulting in increased plasma clearance and a decreased half-life of acetaminophen.

Beta Blockers (Propranolol): Propranolol appears to inhibit the enzyme systems responsible for the glucuronidation and oxidation of acetaminophen. Therefore, the pharmacologic effects of acetaminophen may be increased.

Loop Diuretics: The effects of the loop diuretic may be decreased because acetaminophen may decrease renal prostaglandin excretion and decrease plasma renin activity.

Lamotrigine: Serum lamotrigine concentrations may be reduced, producing a decrease in therapeutic effects.

Probenecid: Probenecid may increase the therapeutic effectiveness of acetaminophen slightly.

Zidovudine: The pharmacologic effects of zidovudine may be decreased because of enhanced nonhepatic or renal clearance of zidovudine.

Carcinogenesis, Mutagenesis, Impairment of Fertility

The mutagenic and carcinogenic potential of propoxyphene and acetaminophen alone and in combination have not been evaluated.

In animal studies there was no effect of propoxyphene on mating behavior, fertility, duration of gestation, or parturition when rats were fed propoxyphene as a component of their daily diet at estimated daily propoxyphene intake up to 8 fold greater than the maximum human equivalent dose (HED) based on body surface area comparison. At this highest dose, fetal weight and survival on postnatal day 4 was reduced. Acetaminophen has not been studied in animals for effects on fertility and the effects on human fertility are unknown.

Pregnancy

Risk Summary

Pregnancy category C

There are no adequate and well-controlled studies of propoxyphene with acetaminophen in pregnant women. While there are limited data in the published literature, adequate animal reproduction studies have not been conducted with propoxyphene or acetaminophen. Therefore, it is not known whether propoxyphene or acetaminophen can affect reproduction or cause fetal harm when administered to a pregnant woman. Propoxyphene with acetaminophen should be given to a pregnant woman only if clearly needed.

Clinical Considerations

Acetaminophen, propoxyphene and its major metabolite, norpropoxyphene, cross the human placenta. Neonates whose mothers have taken opiates chronically may exhibit respiratory depression or withdrawal symptoms.

Data

In published animal reproduction studies, no teratogenic effects occurred in offspring born to pregnant rats or rabbits that received propoxyphene during organogenesis. Pregnant animals received propoxyphene doses approximately 10 fold (rats) and 4 fold (rabbits) the maximum recommended human dose (based on mg/m^2 body surface area comparison).

Nursing Mothers

Propoxyphene, norpropoxyphene (major metabolite), and acetaminophen are excreted in human milk. Published studies of nursing mothers using propoxyphene detected no adverse effects in nursing infants. Based on a study of six mother-infant pairs, an exclusively breastfed infant receives approximately 2% of the maternal weight-adjusted dose. Norpropoxyphene is renally excreted and renal clearance is lower in neonates than in adults. Therefore, it is possible that prolonged maternal propoxyphene use could result in norpropoxyphene accumulation in a breastfed infant. Watch breastfeeding infants for signs of sedation including poor feeding, somnolence, or respiratory depression. Caution should be exercised when propoxyphene napsylate and acetaminophen tablets are administered to a nursing woman.

Pediatric Patients

Safety and effectiveness in pediatric patients have not been established.

Elderly Patients

Clinical studies of propoxyphene napsylate and acetaminophen did not include sufficient numbers of subjects aged 65 and over to determine whether they respond differently from younger subjects. However, postmarketing reports suggest that patients over the age of 65 may be more susceptible to CNS-related side effects. Therefore, dose selection for an elderly patient should be cautious, usually starting at the low end of the dosing range, reflecting the greater frequency of decreased hepatic, renal, or cardiac function, and of concomitant disease or other drug therapy. Decreased total daily dosage should be considered (see DOSAGE AND ADMINISTRATION).

ADVERSE REACTIONS

During clinical trials, the most frequently reported adverse reactions were dizziness, sedation, nausea, and vomiting. Other adverse reactions include constipation, abdominal pain, skin rashes, lightheadedness, headache, weakness, euphoria, dysphoria, hallucinations, and minor visual disturbances.

The most frequently reported postmarketing adverse events have included completed suicide, accidental and intentional overdose, drug dependence, cardiac arrest, coma, drug ineffective, drug toxicity, nausea, respiratory arrest, cardio-respiratory arrest, death, vomiting, dizziness, convulsion, confusional state, and diarrhea.

Additional adverse experiences reported through postmarketing surveillance include:

Cardiac disorders: arrhythmia, bradycardia, cardiac/respiratory arrest, congestive arrest, congestive heart failure (CHF), tachycardia, myocardial infarction (MI)

Eye disorder: eye swelling, vision blurred

General disorder and administration site conditions: drug ineffective, drug interaction, drug tolerance, influenza type illness, drug withdrawal syndrome

Gastrointestinal disorder: gastrointestinal bleed, acute pancreatitis

Hepatobiliary disorder: hepatic steatosis, hepatomegaly, hepatocellular injury

Immune system disorder: hypersensitivity

Injury poisoning and procedural complications: drug toxicity, hip fracture, multiple drug overdose, narcotic overdose

Investigations: blood pressure decreased, heart rate elevated/abnormal

Metabolism and nutrition disorder: metabolic acidosis

Nervous system disorder: ataxia, coma, dizziness, somnolence, syncope

Psychiatric: abnormal behavior, confusional state, hallucinations, mental status change

Respiratory, thoracic, and mediastinal disorders: respiratory depression, dyspnoea

Skin and subcutaneous tissue disorder: rash, itch

Liver dysfunction has been reported in association with both active components of propoxyphene napsylate and acetaminophen tablets. Propoxyphene therapy has been associated with abnormal liver function tests and, more rarely, with instances of reversible jaundice (including cholestatic jaundice). Hepatic necrosis may result from acute overdose of acetaminophen (see OVERDOSAGE). In chronic ethanol abusers, this has been reported rarely with short-term use of acetaminophen dosages of 2.5 to 10 g/day. Fatalities have occurred.

There have also been postmarketing reports of renal papillary necrosis associated with chronic acetaminophen use, particularly when the dosage is greater than recommended and when combined with aspirin. Subacute painful myopathy has been reported following chronic propoxyphene overdosage.

DRUG ABUSE AND DEPENDENCE

Controlled Substance

Propoxyphene napsylate and acetaminophen tablets are a Schedule IV narcotic under the U.S. Controlled Substances Act. Propoxyphene napsylate and acetaminophen tablets can produce drug dependence of the morphine type, and therefore, has the potential for being abused. Psychic dependence, physical dependence and tolerance may develop upon repeated administration. Propoxyphene napsylate and acetaminophen tablets should be prescribed and administered with the same degree of caution appropriate to the use of other narcotic-containing medications.

Abuse

Since propoxyphene napsylate and acetaminophen tablets are a mu-opioid agonist, they may be subject to misuse, abuse, and addiction. Addiction to opioids prescribed for pain management has not been estimated. However, requests for opioids from opioid-addicted patients occur. As such, physicians should take appropriate care in prescribing propoxyphene napsylate and acetaminophen tablets.

Dependence

Opioid analgesics may cause psychological and physical dependence. Physical dependence results in withdrawal symptoms in patients who abruptly discontinue the drug after long term administration. Also, symptoms of withdrawal may be precipitated through the administration of drugs with mu-opioid antagonist activity, e.g., naloxone or mixed agonist/antagonist analgesics (pentazocine, butorphanol, nalbuphine, dezocine) (see OVERDOSAGE). Physical dependence usually does not occur to a clinically significant degree, until after several weeks of continued opioid usage. Tolerance, in which increasingly larger doses are required to produce the same degree of analgesia, is initially manifested by a shortened duration of an analgesic effect and subsequently, by decreases in the intensity of analgesia.

In chronic pain patients, and in opioid-tolerant cancer patients, the administration of propoxyphene napsylate and acetaminophen tablets should be guided by the degree of tolerance manifested and the doses needed to adequately relieve pain.

The severity of the propoxyphene napsylate and acetaminophen tablets abstinence syndrome may depend on the degree of physical dependence. Withdrawal is characterized by rhinitis, myalgia, abdominal cramping, and occasional diarrhea. Most observable symptoms disappear in 5 to 14 days without treatment; however, there may be a phase of secondary or chronic abstinence which may last for 2 to 6 months characterized by insomnia, irritability, and muscular aches. The patient may be detoxified by gradual reduction of the dose. Gastrointestinal disturbances or dehydration should be treated with supportive care.

OVERDOSAGE

Propoxyphene napsylate and acetaminophen tablets are a combination product containing propoxyphene and acetaminophen. Overdose of propoxyphene napsylate and acetaminophen tablets may present with the signs and symptoms of propoxyphene overdose, acetaminophen overdose or both. Fatalities within the first hour of overdosage are not uncommon.

In all cases of suspected overdosage, call your regional Poison Control Center to obtain the most up-to-date information about the treatment of overdose. This recommendation is made because, in general, information regarding the treatment of overdosage may change more rapidly than do package inserts.

Initial consideration should be given to the management of the CNS effects of propoxyphene overdosage. Resuscitative measures should be initiated promptly.

Propoxyphene Overdosage

Symptoms of Propoxyphene Overdosage

The manifestations of acute overdosage with propoxyphene are those of opioid overdosage. The patient is usually somnolent but may be stuporous or comatose and convulsing. Respiratory depression is characteristic. The ventilatory rate and/or tidal volume is decreased, which results in cyanosis and hypoxia. Pupils, initially pinpoint, may become dilated as hypoxia increases. Cheyne-Stokes respiration and apnea may occur. Blood pressure and heart rate are usually normal initially, but blood pressure falls and cardiac performance deteriorates, which ultimately results in pulmonary edema and circulatory collapse, unless the respiratory depression is corrected and adequate ventilation is restored promptly. Cardiac arrhythmias and conduction delay may be present. A combined respiratory-metabolic acidosis occurs owing to retained CO2 (hypercapnia) and to lactic acid formed during anaerobic glycolysis. Acidosis may be severe if large amounts of salicylates have also been ingested. Death may occur.

Treatment of Propoxyphene Overdosage

Attention should be directed first to establishing a patent airway and to restoring ventilation. Mechanically assisted ventilation, with or without oxygen, may be required, and positive pressure respiration may be desirable if pulmonary edema is present. The opioid antagonist naloxone will markedly reduce the degree of respiratory depression, and should be administered promptly, preferably intravenously. The duration of action of the antagonist may be brief. If no response is observed after 10 mg of naloxone have been administered, the diagnosis of propoxyphene toxicity should be questioned.

In addition to the use of an opioid antagonist, the patient may require careful titration with an anticonvulsant to control convulsions. Activated charcoal can adsorb a significant amount of ingested propoxyphene. Dialysis is of little value in poisoning due to propoxyphene. Efforts should be made to determine whether other agents, such as alcohol, barbiturates, tranquilizers, or other CNS depressants, were also ingested, since these increase CNS depression as well as cause specific toxic effects or death.

Acetaminophen Overdosage

Symptoms of Acetaminophen Overdosage

Overdose of acetaminophen may cause dose-dependent potentially fatal hepatic toxicity. Early symptoms within 24 hours after the overdose may include anorexia, nausea, vomiting, diaphoresis, general malaise, and abdominal pain. The patient may then present no symptoms, but evidence of liver dysfunction may become apparent up to 72 hours after ingestion, with elevated serum transaminase and lactic dehydrogenase levels, an increase in serum bilirubin concentrations, and a prolonged prothrombin time. Death from hepatic failure may result 3 to 7 days after overdosage.

Because clinical and laboratory evidence of hepatic toxicity may not be apparent until 48 to 72 hours post-ingestion, liver function studies should be obtained initially and repeated at 24 hour intervals.

Acute renal failure may accompany the hepatic dysfunction and has been noted in patients who do not exhibit signs of fulminant hepatic failure. Typically, renal impairment is more apparent 6 to 9 days after ingestion of the overdose.

Treatment of Acetaminophen Overdosage

In all cases of suspected overdose, immediately call the Rocky Mountain Poison Center's toll-free number (800-525-6115) for assistance in diagnosis and for directions in the use of N-acetylcysteine as an antidote.

Patients' estimates of the quantity of a drug ingested are notoriously unreliable. Therefore, if an acetaminophen overdose is suspected, a serum acetaminophen assay should be obtained as early as possible, but no sooner than 4 hours following ingestion. The antidote, N-acetylcysteine, should be administered as early as possible, and within 16 hours of the overdose ingestion for optimal results.

DOSAGE AND ADMINISTRATION

Proproxyphene napsylate and acetaminophen tablets USP are intended for the management of mild to moderate pain. The dose should be individually adjusted according to severity of pain, patient response and patient size.

Propoxyphene napsylate and acetaminophen tablets USP (100 mg propoxyphene napsylate and 650 mg acetaminophen)

The usual dosage is one tablet every 4 hours orally as needed for pain. The maximum dose of propoxyphene napsylate and acetaminophen tablets USP is 6 tablets per day. Do not exceed the maximum daily dose.

Patients receiving propoxyphene and any CYP3A4 inhibitor should be carefully monitored for an extended period of time and dosage adjustments should be made if warranted.

Consideration should be given to a reduced total daily dosage in elderly patients and in patients with hepatic or renal impairment.

Cessation of Therapy

For patients who used propoxyphene napsylate and acetaminophen tablets USP on a regular basis for a period of time, when therapy with propoxyphene napsylate and acetaminophen tablets USP is no longer needed for the treatment of their pain, it may be useful to gradually discontinue the propoxyphene napsylate and acetaminophen tablets USP over time to prevent the development of an opioid abstinence syndrome (narcotic withdrawal). In general, therapy can be decreased by 25% to 50% per day with careful monitoring for signs and symptoms of withdrawal (see DRUG ABUSE AND DEPENDENCE for description of the signs and symptoms of withdrawal). If the patient develops these signs or symptoms, the dose should be raised to the previous level and titrated down more slowly, either by increasing the interval between decreases, decreasing the amount of change in dose, or both.

HOW SUPPLIED

Propoxyphene napsylate and acetaminophen tablets, USP 100 mg/650 mg (PINK) are available as film-coated, oblong, pink tablets debossed either "93"-"890" or "TEVA"-"890", in bottles of 100 and 500 tablets.

Propoxyphene napsylate and acetaminophen tablets, USP 100 mg/650 mg (WHITE) are available as film-coated, oblong, white tablets debossed either "93"-"490" or "TEVA"-"490", in bottles of 100 and 500 tablets.

Store at 20° to 25°C (68° to 77°F) [See USP Controlled Room Temperature].

Inform patients of the availability of a Medication Guide for propoxyphene napsylate and acetaminophen tablets USP that accompanies each prescription dispensed. Instruct patients to read the propoxyphene napsylate and acetaminophen Medication Guide prior to using propoxyphene napsylate and acetaminophen tablets USP.

TEVA PHARMACEUTICALS USA

Sellersville, PA 18960

Rev. W 10/2009

MEDICATION GUIDE

PROPOXYPHENE NAPSYLATE AND ACETAMINOPHEN TABLETS USP CIV

Rx only

Read this Medication Guide before you start taking propoxyphene napsylate and acetaminophen tablets USP and each time you get a refill. There may be new information. This information does not take the place of talking to your doctor about your medical condition or your treatment.

What is the most important information I should know about propoxyphene napsylate and acetaminophen tablets USP?

Propoxyphene napsylate and acetaminophen tablets USP and other medicines that contain propoxyphene can cause serious side effects, including:

Overdoses by accident or on purpose (intentional overdose). Overdoses with propoxyphene napsylate and acetaminophen tablets USP may happen when they are taken by themselves, or with alcohol or other medicines that can also decrease your breathing and make you very sleepy.

- Death can happen within 1 hour of taking an overdose of propoxyphene napsylate and acetaminophen tablets USP. Many of the deaths that happen in people who take propoxyphene napsylate and acetaminophen tablets USP happen in those who:
  - have emotional problems
  - have thoughts of suicide or attempted suicide, or
  - also take antidepressants, sedatives, tranquilizers, muscle relaxants, or other medicines that affect your breathing and make you very sleepy. You should not use any of these medicines with propoxyphene napsylate and acetaminophen tablets USP without talking to your doctor.
- Before taking propoxyphene napsylate and acetaminophen tablets USP tell your doctor if you:
  - have a lung problem, such as COPD or cor pulmonale
  - have liver or kidney problems
  - have problems with your pancreas or gallbladder
  - have a history of head injury
  - are over age 65
  - have a history of drug or alcohol abuse or addiction

Take propoxyphene napsylate and acetaminophen tablets USP exactly as prescribed. Do not change your dose or stop taking propoxyphene napsylate and acetaminophen tablets USP without first talking to your doctor.

-
  - If you take propoxyphene napsylate and acetaminophen tablets USP, 100 mg/650 mg do not take more than 6 tablets in one day.
- Before taking propoxyphene napsylate and acetaminophen tablets USP, tell your doctor about all the medicines you take. Propoxyphene napsylate and acetaminophen tablets USP and many other medicines may interact with each other and may cause serious side effects. Certain medicines can affect how your liver breaks down other medicines. See "What should I tell my doctor before taking propoxyphene napsylate and acetaminophen tablets USP?"
- Do not drink grapefruit juice or eat grapefruit while you are taking propoxyphene napsylate and acetaminophen tablets USP. Grapefruit juice may interact with propoxyphene napsylate and acetaminophen tablets USP.
- Do not drink alcohol while using propoxyphene napsylate and acetaminophen tablets USP. Using alcohol with propoxyphene napsylate and acetaminophen tablets USP may increase your risk of having dangerous side effects.

What are propoxyphene napsylate and acetaminophen tablets USP?

- Propoxyphene napsylate and acetaminophen tablets USP are a prescription medicine that contains two medicines: propoxyphene and acetaminophen. Propoxyphene napsylate and acetaminophen tablets USP are used to relieve mild to moderate pain.

BOXED WARNING

- Propoxyphene napsylate and acetaminophen tablets USP are a federally controlled substance (C-IV) because they are a strong opioid pain medicine that can be abused by people who abuse prescription medicines or street drugs.
- Prevent theft, misuse or abuse. Keep propoxyphene napsylate and acetaminophen tablets USP in a safe place to protect it from being stolen. Propoxyphene napsylate and acetaminophen tablets USP can be a target for people who misuse or abuse prescription medicines or street drugs.
- Never give propoxyphene napsylate and acetaminophen tablets USP to anyone else, even if they have the same symptoms that you have. It may harm them or even cause death. Selling or giving away this medicine is against the law.

It is not known if propoxyphene napsylate and acetaminophen tablets USP are safe and effective in children under age 18.

Who should not take propoxyphene napsylate and acetaminophen tablets USP?

Do not take propoxyphene napsylate and acetaminophen tablets USP if you:

- are allergic to propoxyphene or acetaminophen. Ask your doctor if you are not sure. See the end of this Medication Guide for a list of the ingredients in propoxyphene napsylate and acetaminophen tablets USP.
- are having an asthma attack or have severe asthma, trouble breathing, or lung problems.
- have a bowel blockage called paralytic ileus.

What should I tell my doctor before taking propoxyphene napsylate and acetaminophen tablets USP?

Before taking propoxyphen napsylate and acetaminophen tablets USP, tell your doctor:

- if you have any of the conditions listed in the section "What is the most important information I should know about propoxyphene napsylate and acetaminophen tablets USP?"
- if you are allergic to propoxyphene or acetaminophen
- if you plan to have surgery with general anesthesia
- if you are pregnant or plan to become pregnant.
- if you take propoxyphene napsylate and acetaminophen tablets USP regularly before your baby is born, your newborn baby may have withdrawal symptoms because their body has become used to the medicine. Symptoms of withdrawal in a newborn baby may include:
  - irritability
  - shaking (tremors)
  - jitteriness
  - breathing faster than normal
  - crying more than usual
  - diarrhea or more stools than normal
  - vomiting
  - fever
- if you take propoxyphene napsylate and acetaminophen tablets USP right before your baby is born, your baby could have breathing problems.
- if you are breast-feeding or plan to breast-feed. Some propoxyphene napsylate and acetaminophen passes into breast milk.

Tell your doctor about all the medicines you take, including prescription, and non-prescription medicines, vitamins, and herbal supplements. Propoxyphene napsylate and acetaminophen tablets USP interact with many medicines and may lead to serious side effects. The doses of certain medicines may need to be changed.

Especially tell your doctor if you take:

See "What is the most important information I should know about propoxyphene napsylate and acetaminophen tablets USP?"

- certain medicines that can affect how your liver breaks down other medicines.
- a monoamine oxidase inhibitor (MAOI) medicine
- other medicines that make you sleepy, such as: other medicines for pain, including other opioid medicines, anti-depressant medicines, sleeping pills, anti-anxiety medicines, muscle relaxants, anti-nausea medicines, or tranquilizers
- an anticholinergic medicine
- a water pill (diuretic)
- a medicine for high blood pressure or irregular heart beat
- birth control pills taken by mouth
- lamotrigine (Lamictal®, Lamictal® CD™, Lamictal® XR™, Lamictal® ODT™)
- probenecid (Probalan®)
- a blood-thinner medicine. You may have an increased risk of bleeding while also taking propoxyphene napsylate and acetaminophen tablets USP.
- zidovudine (Trizivir®, Combivir®, Retrovir®)

Do not take other medicines that contain acetaminophen while taking propoxyphene napsylate and acetaminophen tablets USP. See "What are the possible side effects of propoxyphene napsylate and acetaminophen tablets USP?"

Ask your doctor or pharmacist if you are not sure if your medicine is one listed above.

Know the medicines you take. Keep a list of them to show to your doctor and pharmacist when you get a new medicine.

How should I take propoxyphene napsylate and acetaminophen tablets USP?

See "What is the most important information I should know about propoxyphene napsylate and acetaminophen tablets USP?"

- Take propoxyphene napsylate and acetaminophen tablets USP exactly as prescribed.
- If you take too many propoxyphene napsylate and acetaminophen tablets USP, or take it with alcohol or other medicines, you may overdose. See "What is the most important information I should know about propoxyphene napsylate and acetaminophen tablets USP?". You will need medical help right away if you think you have taken an overdose of propoxyphene napsylate and acetaminophen tablets USP. A large overdose can cause you to become unconscious and die.

Signs and symptoms of an overdose of propoxyphene napsylate and acetaminophen tablets USP include:

- you are very sleepy or do not respond to others
- confusion
- have trouble breathing or stop breathing
- changes in blood pressure and heart rate
- nausea
- vomiting
- loss of appetite
- stomach-area (abdominal pain)

What are the possible side effects of propoxyphene napsylate and acetaminophen tablets USP?

Propoxyphene napsylate and acetaminophen tablets USP can cause serious side effects, including:

See "What is the most important information I should know about propoxyphene napsylate and acetaminophen tablets USP?"

- Serious breathing problems that can become life-threatening. This is especially true if you already have a serious lung or breathing problem, or your body is not used to opioid pain medicines. This can happen even if you take propoxyphene napsylate and acetaminophen tablets USP exactly as prescribed by your doctor. Call your doctor or get medical help right away if:
  - your breathing slows down
  - you have shallow breathing (little chest movement with breathing)
  - you feel faint, dizzy, confused, or
  - you have any other unusual symptoms
- Propoxyphene napsylate and acetaminophen tablets USP can cause your blood pressure to drop. This can make you feel dizzy and faint if you get up too fast from sitting or lying down. Low blood pressure is also more likely to happen if you take other medicines that can also lower your blood pressure. Severe low blood pressure can happen if you lose blood or take certain other medicines.
- Liver problems. Propoxyphene napsylate and acetaminophen tablets USP contain acetaminophen. Acetaminophen can cause serious liver problems if you take more than the recommended dose. Do not take more propoxyphene napsylate and acetaminophen tablets USP than prescribed. See "How should I take propoxyphene napsylate and acetaminophen tablets USP?" Do not take any other medicines that contain acetaminophen while also taking propoxyphene napsylate and acetaminophen tablets USP. Many products contain acetaminophen. Ask your doctor or pharmacist if you are not sure. Liver damage may happen even after symptoms go away. You can die from liver failure days later. Tell your doctor if you have any of these symptoms of a liver problem while taking propoxyphene napsylate and acetaminophen tablets USP:
  - nausea
  - vomiting
  - loss of appetite
  - stomach area (abdominal pain)
- Sleepiness. Propoxyphene napsylate and acetaminophen tablets USP can cause sleepiness and may affect your ability to make decisions, think clearly, or react quickly. Do not drive, operate heavy machinery, or do other dangerous activities until you know how propoxyphene napsylate and acetaminophen tablets USP affect you.
- Propoxyphene napsylate and acetaminophen tablets USP can cause physical dependence if you take them for more than a few weeks. Do not stop taking propoxyphene napsylate and acetaminophen tablets USP all of a sudden. You could become sick with uncomfortable withdrawal symptoms (for example, nausea, vomiting, diarrhea, anxiety, and shivering) because your body has become used to the medicine. Talk to your doctor about slowly stopping propoxyphene napsylate and acetaminophen tablets USP to avoid getting sick with withdrawal symptoms. Physical dependence is not the same as drug addiction. Your doctor can tell you more about the differences between physical dependence and drug addiction.
  Tell your doctor if you have any of these withdrawal symptoms while you slowly stop taking propoxyphene napsylate and acetaminophen tablets USP. You may need to stop propoxyphene napsylate and acetaminophen tablets USP more slowly.

Common side effects of propoxyphene napsylate and acetaminophen tablets USP include:

-
  - dizziness
  - feeling sleepy
  - nausea and vomiting
  - constipation
  - stomach area (abdominal) pain
  - skin rashes
  - lightheadedness
  - headache
  - weakness
  - feeling of excitement (elation) or discomfort
  - seeing, hearing, or sensing things that are not really there (hallucinations)
  - blurred vision

Call your doctor for medical advice about side effects. You may report side effects to FDA at 1-800-FDA-1088.

You may also report side effects to TEVA USA, PHARMACOVIGILANCE at 1-888-838-2872, X6351.

How should I store propoxyphene napsylate and acetaminophen tablets USP?

- Store propoxyphene napsylate and acetaminophen tablets USP at 20° to 25°C (68° to 77°F).

Keep propoxyphene napsylate and acetaminophen tablets USP and all medicines out of the reach of children.

General information about propoxyphene napsylate and acetaminophen tablets USP

Medicines are sometimes prescribed for purposes other than those listed in a Medication Guide. Do not use propoxyphene napsylate and acetaminophen tablets USP for a purpose for which they were not prescribed. Do not give propoxyphene napsylate and acetaminophen tablets USP to others even if they have the same symptoms you have. It may harm them and is against the law. This Medication Guide summarizes the most important information about propoxyphene napsylate and acetaminophen tablets USP. If you would like more information, talk with your doctor. You can ask your pharmacist or doctor for information about propoxyphene napsylate and acetaminophen tablets USP that is written for health professionals. For more information, call 1-888-838-2872, MEDICAL AFFAIRS.

What are the ingredients in propoxyphene napsylate and acetaminophen tablets USP?

Active ingredients: propoxyphene napsylate and acetaminophen

Propoxyphene napsylate and acetaminophen tablets, USP 100 mg/650 mg (PINK) contain the following inactive ingredients: colloidal silicon dioxide, D&C Red No. 27 aluminum lake, D&C Yellow No. 10 aluminum lake, hydroxypropyl cellulose, hypromellose, magnesium stearate, microcrystalline cellulose, polyethylene glycol, povidone, pregelatinized starch, stearic acid, titanium dioxide, and crospovidone.

Propoxyphene napsylate and acetaminophen tablets, USP 100 mg/650 mg (WHITE) contain the following inactive ingredients: castor oil, colloidal silicon dioxide, hypromellose, magnesium stearate, microcrystalline cellulose, povidone, pregelatinized starch, stearic acid, and crospovidone.

This Medication Guide has been approved by the U.S. Food and Drug Administration.

All brand names listed are the registered trademarks of their respective owners and are not trademarks of Teva Pharmaceuticals USA.

TEVA PHARMACEUTICALS USA

Sellersville, PA 18960

Iss. 10/2009

copy of label